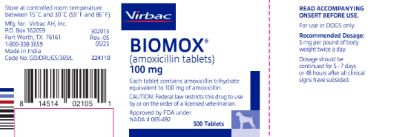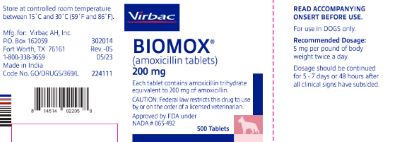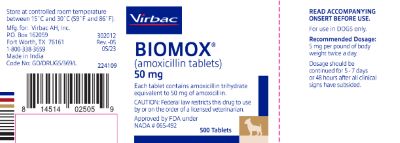 DRUG LABEL: Biomox
NDC: 51311-201 | Form: TABLET
Manufacturer: Virbac AH, Inc.
Category: animal | Type: PRESCRIPTION ANIMAL DRUG LABEL
Date: 20240826

ACTIVE INGREDIENTS: amoxicillin 50 mg/1 1

Approved by FDA under NADA # 065-492
BIOMOX® (amoxicillin tablets)

For use in DOGS only.

DESCRIPTION:

BIOMOX® (amoxicillin tablets) are a broad-spectrum, semisynthetic antibiotic which provides bactericidal activity against a wide range of common gram-positive and gram-negative pathogens. Amoxicillin chemically is D-(-)α-amino-p-hydroxybenzyl penicillin trihydrate.

Inactive Ingredients:

Dibasic Calcium Phosphate Dihydrate, Magnesium Stearate, Microcrystalline Cellulose and Sodium Starch Glycolate.

ACTION:

Amoxicillin has bactericidal activity against susceptible organisms similar to that of ampicillin. It acts by inhibiting the biosynthesis of bacterial cell wall mucopeptides. Most strains of the following gram-positive and gram-negative bacteria have demonstrated susceptibility to amoxicillin, both in vitro and in vivo: nonpenicillinase-producing staphylococci, alpha- and beta- hemolytic streptococci, Enterococcus faecalis, Escherichia coli and Proteus mirabilis. Amoxicillin does not resist destruction by penicillinase; therefore, it is not effective against penicillinase-producing bacteria, particularly resistant staphylococci. Most strains of Enterobacter and Klebsiella and all strains of Pseudomonas are resistant.

Amoxicillin may be given without regard to meals because it is stable in gastric acid. It is rapidly absorbed following oral administration and diffuses readily into most body fluids and tissues. It diffuses poorly into the brain and spinal fluid except when the meninges are inflamed. Most of the amoxicillin is excreted in the urine unchanged.

INDICATIONS:

BIOMOX® (amoxicillin tablets) are indicated for treatment of the following infections in dogs when caused by susceptible strains of organisms:

BACTERIAL DERMATITIS due to Staphylococcus aureus, Strepto-coccus spp., Staphylococcus spp., and Escherichia coli.

SOFT TISSUE INFECTIONS (abscesses, wounds, lacerations) due to Staphylococcus aureus,Enterococcus faecalis, Escherichia coli, Proteus mirabilis, and Staphylococcus spp.

With all antibiotic therapy, appropriate in vitro cultures and sensitivities should be conducted prior to treatment.

CONTRAINDICATIONS:

Use of amoxicillin is contraindicated in animals with a history of an allergic reaction to penicillin.

ADVERSE REACTIONS:

Amoxicillin is a semisynthetic penicillin and, therefore, has the potential for producing allergic reactions. Epinephrine and/or steroids should be administered if an allergic reaction occurs.

WARNINGS:

For use in dogs only.

PRECAUTIONS:

Until adequate reproductive studies are accomplished, Biomox® (amoxicillin tablets) should not be used in pregnant or breeding animals.

CAUTION:

Federal law restricts this drug to use by or on the order of a licensed veterinarian.

DOSAGE AND ADMINISTRATION:

The recommended dosage is 5 mg per pound of body weight administered twice daily for 5 to 7 days or 48 hours after all symptoms have subsided. If no improvement is noted in 5 days, the diagnosis should be reconsidered and therapy changed.

SUPPLY:

Biomox® (amoxicillin tablets) are supplied in 50 mg, 100 mg and 200 mg concentrations in bottles of 500 tablets.

STATEMENT OF IDENTITY

Manufactured for:
Virbac AH, Inc.
P.O. Box 162059
Fort Worth, TX 76161
1-800-338-3659

Printed in USA Rev. -06 05/23

©2023 Virbac Corporation. All Rights Reserved. BIOMOX is a registered trademark of the Virbac Group of Companies.